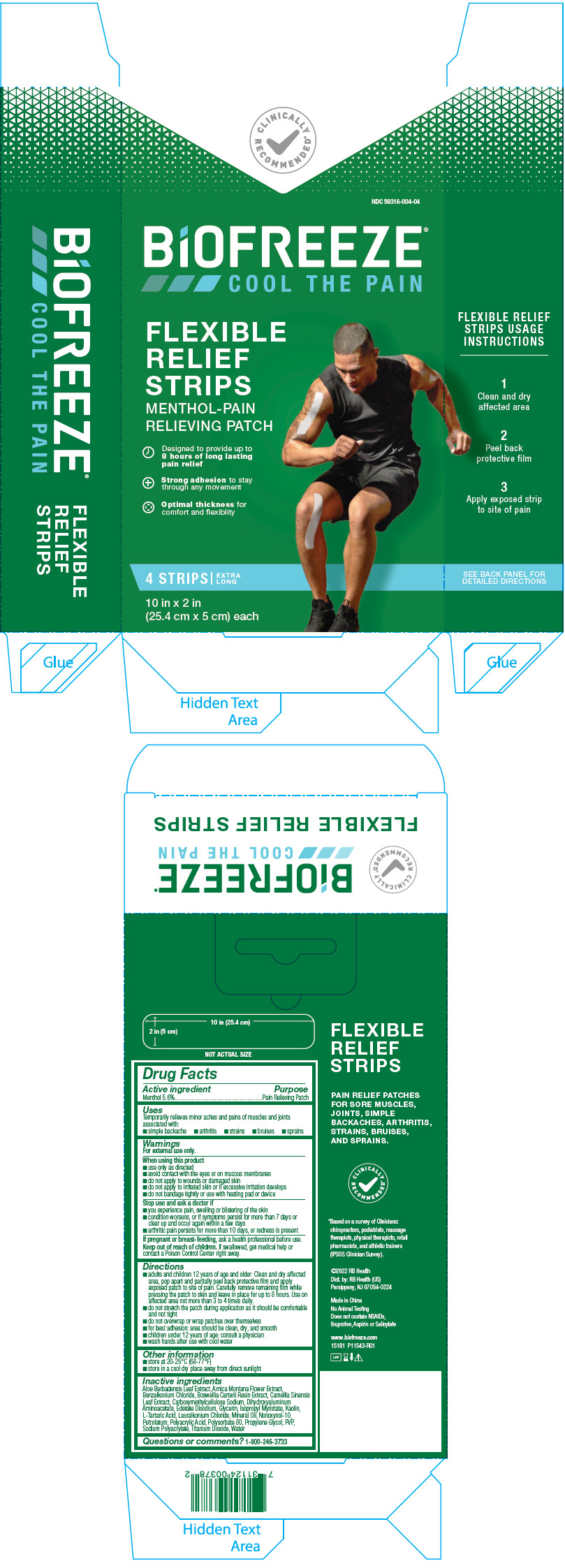 DRUG LABEL: Biofreeze Flexible Relief Strip
NDC: 59316-004 | Form: PATCH
Manufacturer: RB Health (US) LLC
Category: otc | Type: HUMAN OTC DRUG LABEL
Date: 20241227

ACTIVE INGREDIENTS: MENTHOL, UNSPECIFIED FORM 56 mg/1 g
INACTIVE INGREDIENTS: ALOE VERA LEAF; ARNICA MONTANA FLOWER; BENZALKONIUM CHLORIDE; FRANKINCENSE; GREEN TEA LEAF; CARBOXYMETHYLCELLULOSE SODIUM, UNSPECIFIED; DIHYDROXYALUMINUM AMINOACETATE; EDETATE DISODIUM; GLYCERIN; ISOPROPYL MYRISTATE; KAOLIN; TARTARIC ACID; LAURALKONIUM CHLORIDE; MINERAL OIL; NONOXYNOL-10; PETROLATUM; POLYSORBATE 80; PROPYLENE GLYCOL; POVIDONE, UNSPECIFIED; TITANIUM DIOXIDE; WATER

Biofreeze®Flexible Relief Strip

Drug Facts

Active ingredient

Menthol 5.6%

Purpose

Pain Relieving Patch

Uses

Temporarily relieves minor aches and pains of muscles and joints associated with:

- simple backache
- arthritis
- strains
- bruises
- sprains

Warnings

For external use only.

When using this product

- use only as directed
- avoid contact with the eyes or on mucous membranes
- do not apply to wounds or damaged skin
- do not apply to irritated skin or if excessive irritation develops
- do not bandage tightly or use with heating pad or device

Stop use and ask a doctor if

- you experience pain, swelling or blistering of the skin
- condition worsens, or if symptoms persist for more than 7 days or clear up and occur again within a few days
- arthritic pain persists for more than 10 days, or redness is present

PREGNANCY OR BREAST FEEDING

If pregnant or breast-feeding,ask a health professional before use.

Keep out of reach of children.If swallowed, get medical help or contact a Poison Control Center right away.

Directions

- adults and children 12 years of age and older: Clean and dry affected area, pop apart and partially peel back protective film and apply exposed patch to site of pain. Carefully remove remaining film while pressing the patch to skin and leave in place for up to 8 hours. Use on affected area not more than 3 to 4 times daily.
- do not stretch the patch during application as it should be comfortable and not tight
- do not overwrap or wrap patches over themselves
- for best adhesion: area should be clean, dry, and smooth
- children under 12 years of age: consult a physician
- wash hands after use with cool water

Other information

- store at 20-25°C (68-77°F)
- store in a cool dry place away from direct sunlight

Inactive ingredients

Aloe Barbadensis Leaf Extract, Arnica Montana Flower Extract, Benzalkonium Chloride, Boswellia Carterii Resin Extract, Camellia Sinensis Leaf Extract, Carboxymethylcellulose Sodium, Dihydroxyaluminum Aminoacetate, Edetate Disodium, Glycerin, Isopropyl Myristate, Kaolin, L-Tartaric Acid, Lauralkonium Chloride, Mineral Oil, Nonoxynol-10, Petrolatum, Polyacrylic Acid, Polysorbate 80, Propylene Glycol, PVP, Sodium Polyacrylate, Titanium Dioxide, Water

Questions or comments?

1-800-246-3733

Dist. by: RB Health (US)
Parsippany, NJ 07054-0224

PRINCIPAL DISPLAY PANEL - 4 Strip Carton

CLINICALLY
RECOMMENDED*

NDC 59316-004-04

BiOFREEZE®
COOL THE PAIN

FLEXIBLE
RELIEF
STRIPS
MENTHOL-PAIN
RELIEVING PATCH

Designed to provide up to
8 hours of long lasting
pain relief

Strong adhesion to stay
through any movement

Optimal thickness for
comfort and flexiblity

4 STRIPS |
EXTRA
LONG

10 in x 2 in
(25.4 cm x 5 cm) each